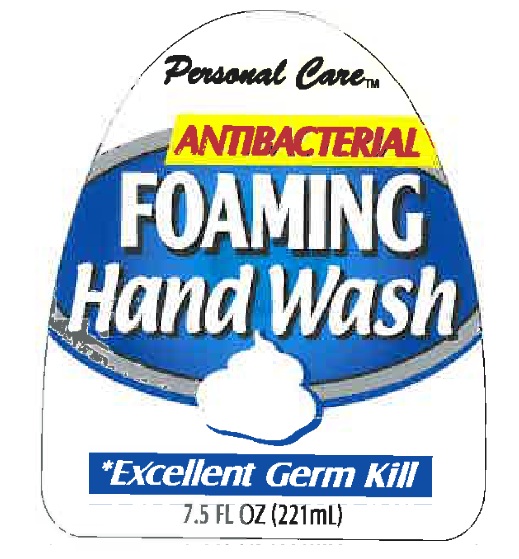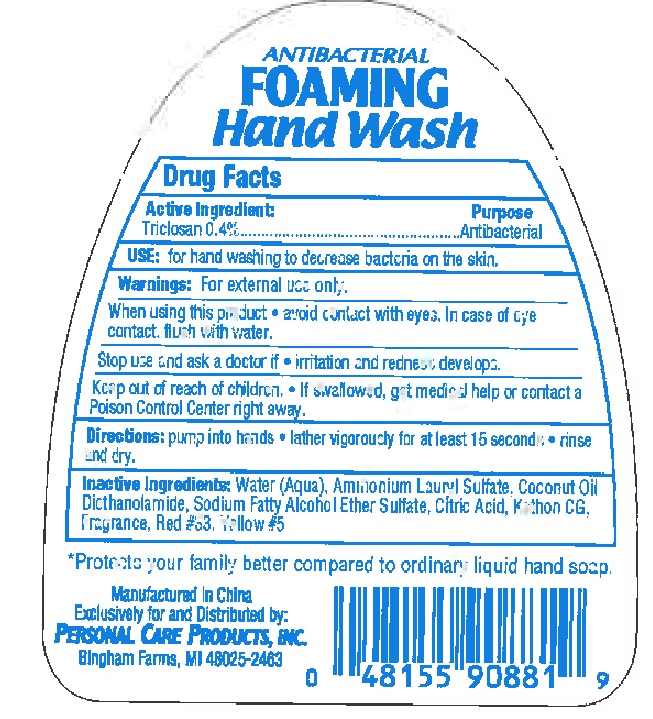 DRUG LABEL: Personal Care Antibacterial Foaming Hand Wash
NDC: 29500-0881 | Form: LIQUID
Manufacturer: Personal Care Products, LLC
Category: otc | Type: HUMAN OTC DRUG LABEL
Date: 20110810

ACTIVE INGREDIENTS: TRICLOSAN 0.4 mL/100 mL
INACTIVE INGREDIENTS: WATER; AMMONIUM LAURYL SULFATE; COCONUT OIL; CITRIC ACID MONOHYDRATE; FD&C YELLOW NO. 5; DIETHANOLAMINE; ALCOHOL; ETHER; SULFATE ION

Personal Care Antibacterial Foaming Hand Wash

Active Ingredient Purpose

Triclosan 0.4% Antibacterial

Purpose

Antibacterial

INDICATIONS AND USAGE

Uses: For hand washing to decrease bacteria on the skin.

Warnings

For external use only.

When using this product avoid contact with eyes. In case of eye contact, flush with water.

Stop use and ask a doctor if irritation and redness develops

Keep out of reach of children. If swallowed, get medical help or contact a Poison Control Center right away.

Directions

pump into hands
lather vigorously for at least 15 seconds
rinse and dry

Inactive Ingredients

water (aqua), ammonium laryl sulfate, coconut oil, diethanolamide, sodium fatty alcohol ether sulfate, citric acid, kathon CG, Fragrance, Red #33, Yellow#5

DESCRIPTION

Protects your family better compared to ordinary liquid hand soap.

Manufactured in China

Exclusively for and Distributed by:

Personal Care Products, Inc.

Bingham Farms, MI 48025-2463

PACKAGE LABEL

Personal Care

Antibacterial Foaming Hand wash
Excellent germ kill
7.5 fl oz (221ml)